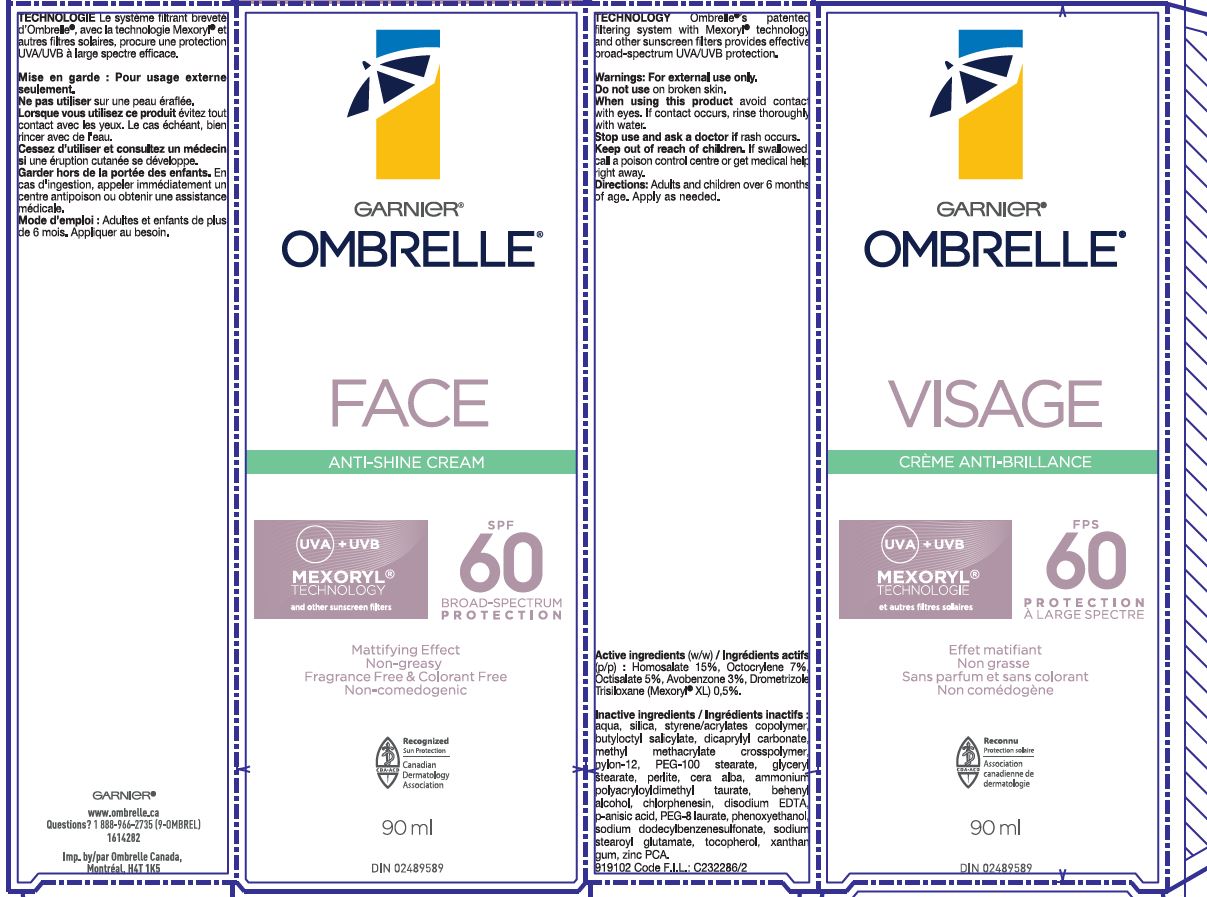 DRUG LABEL: Garnier Ombrelle Face Anti-Shine SPF 60 Mexoryl Technology
NDC: 49967-209 | Form: LOTION
Manufacturer: L'Oreal USA Products Inc
Category: otc | Type: HUMAN OTC DRUG LABEL
Date: 20260107

ACTIVE INGREDIENTS: HOMOSALATE 150 mg/1 mL; OCTOCRYLENE 70 mg/1 mL; OCTISALATE 50 mg/1 mL; AVOBENZONE 30 mg/1 mL; DROMETRIZOLE TRISILOXANE 5 mg/1 mL
INACTIVE INGREDIENTS: WATER; SILICON DIOXIDE; BUTYLOCTYL SALICYLATE; DICAPRYLYL CARBONATE; METHYL METHACRYLATE/GLYCOL DIMETHACRYLATE CROSSPOLYMER; NYLON-12; PEG-100 STEARATE; GLYCERYL MONOSTEARATE; PERLITE; WHITE WAX; AMMONIUM POLYACRYLOYLDIMETHYL TAURATE (55000 MPA.S); DOCOSANOL; CHLORPHENESIN; P-ANISIC ACID; TOCOPHEROL; SODIUM STEAROYL GLUTAMATE; PHENOXYETHANOL; PEG-8 LAURATE; XANTHAN GUM; EDETATE DISODIUM; SODIUM DODECYLBENZENESULFONATE; ZINC PIDOLATE

Drug Facts

Active ingredients

Homosalate 15%

Octocrylene 7%

Octisalate 5%

Avobenzone 3%

Drometrizole Trisiloxane 0.5%

Inactive ingredients

aqua, silica, styrene/acrylates copolymer, butyloctyl salicylate, dicaprylyl carbonate, methyl methacrylate copolymer, nylon-12, PEG-100 stearate, glyceryl stearate, perlite, cera alba, ammonium polyacryloyldimethyl taurate, behenyl alcohol, chlorphenesin, disodium EDTA, p-anisic acid, PEG-8 laurate, phenoxyethanol, sodium dodecylbenzenesulfonate, sodium stearoyl glutamate, tocopherol, xanthan gum, zinc PCA

Warnings

For external use only

Do not use

on damaged or broken skin

When using this product

avoid contact with eyes. If contact occurs, rinse thoroughly with water.

Stop use and ask a doctor if

rash occurs

Keep out of reach of children.

If swallowed, get medical help or contact a poison control center right away.

Directions

Adults and children 6 months and up. Apply as needed